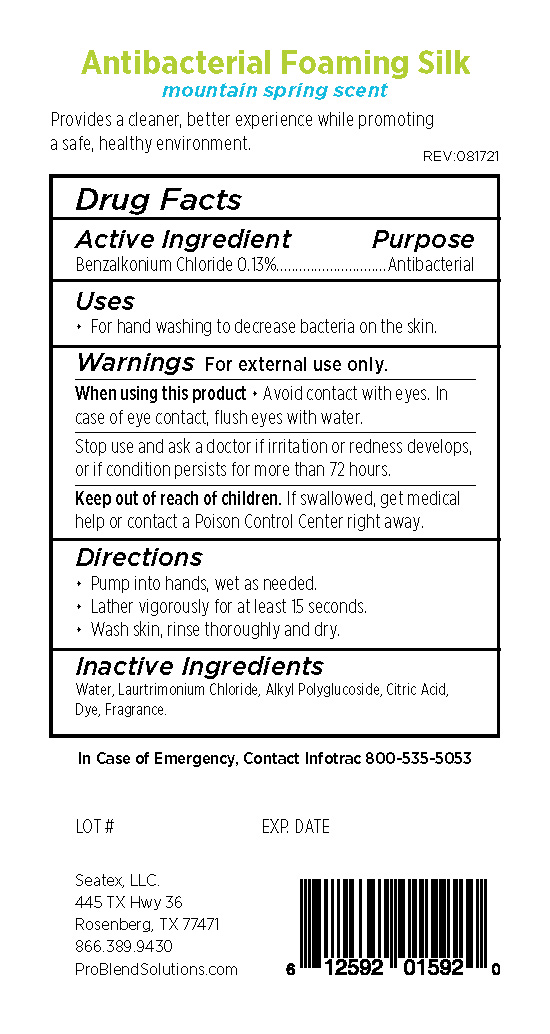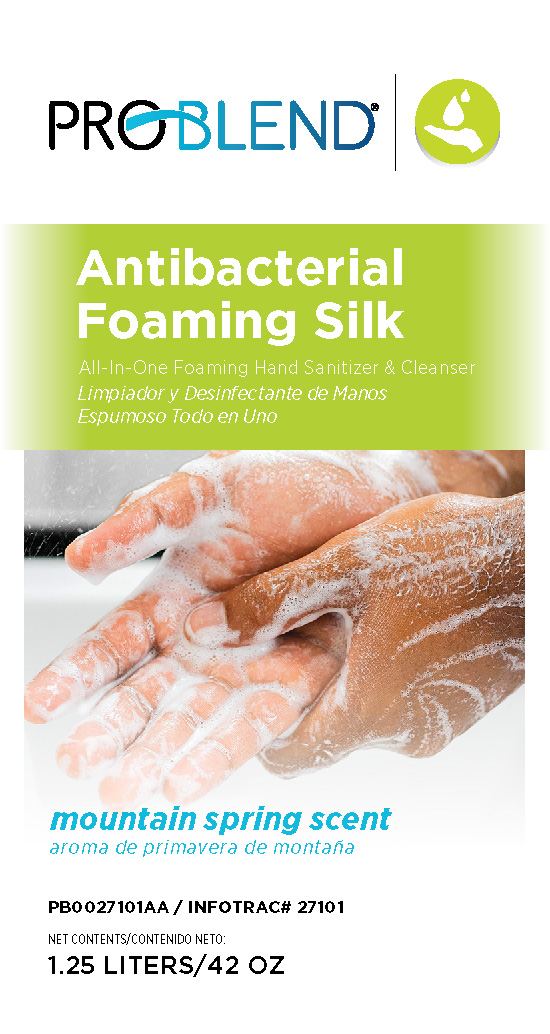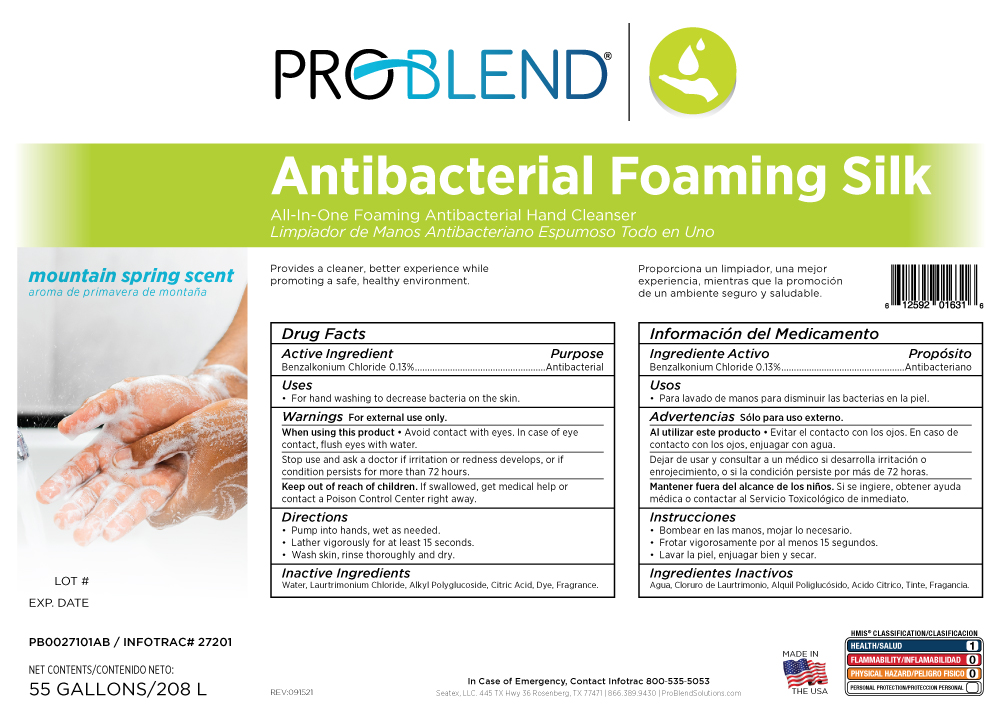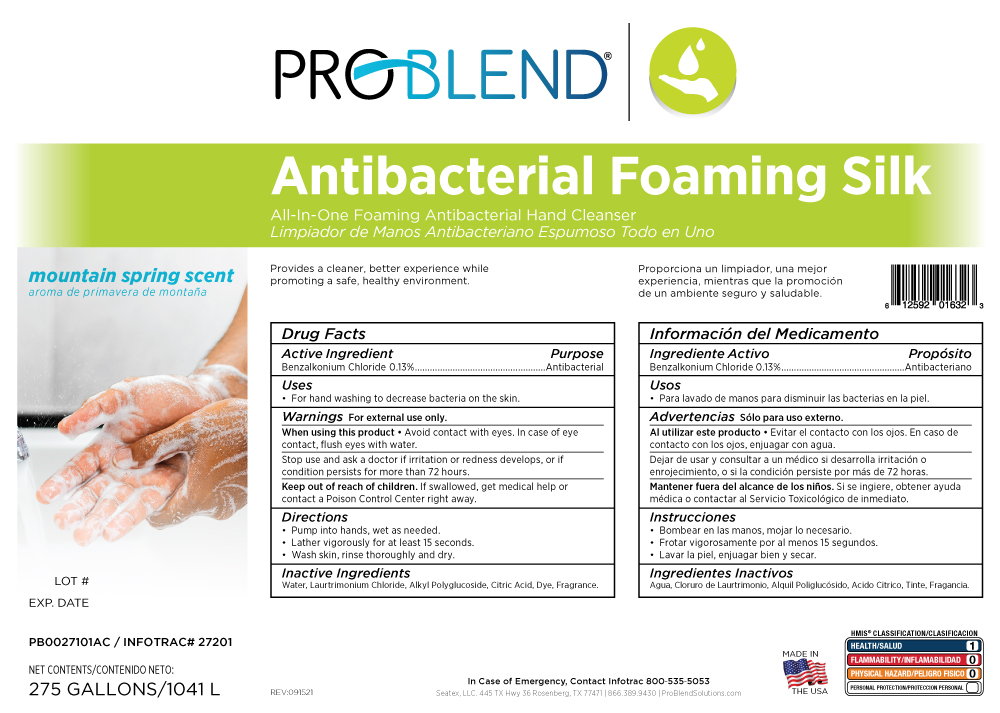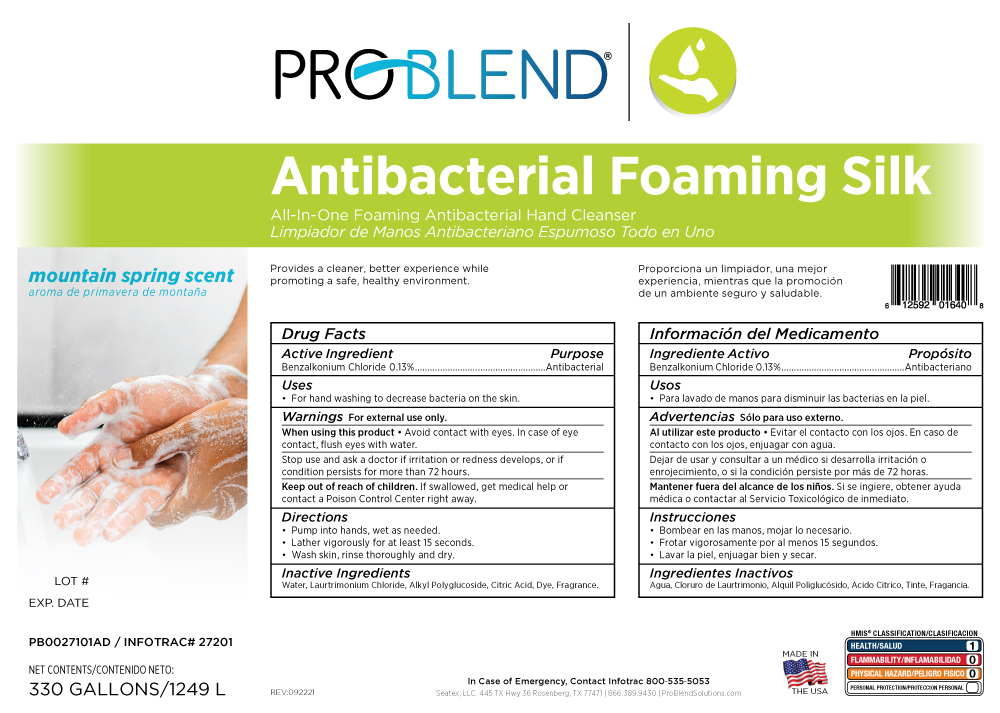 DRUG LABEL: Problend Antibacterial Foaming Silk
NDC: 76250-101 | Form: SOAP
Manufacturer: Seatex LLC
Category: otc | Type: HUMAN OTC DRUG LABEL
Date: 20220919

ACTIVE INGREDIENTS: BENZALKONIUM CHLORIDE 0.13 g/100 g
INACTIVE INGREDIENTS: WATER; LAURTRIMONIUM CHLORIDE; CAPRYLYL/CAPRYL OLIGOGLUCOSIDE; FD&C BLUE NO. 1; FRAGRANCE CLEAN ORC0600327; CITRIC ACID MONOHYDRATE

27101 Problend

Active Ingredient Purpose

Benzalkonium Chloride 0.13%............Antibacterial

Uses

For hand washing to decrease bacteria on the skin.

Warnings For external use only.

When using this product Avoid contact with eyes. In case of eye contact, flush eyes with water.

Stop use and ask a doctor if irritation or redness develops. or if condition persists for more than 72 hours.

Keep out of reach of children. If swallowed, get medical help or contact a Poison Contdrol Center right away.

Directions

Pump into hands, wet as needed.

Lather vigorously for at least 15 seconds.

Wash skin, rinse thoroughly and dry.

Inactive Ingredients

Water, Laurtrimonium Chloride, Alkyl Polyglucoside, Citric Acid, Dye, Fragrance.

PURPOSE

Antiseptic, Hand Sanitizer

PACKAGE LABEL

1.25 L 76250-101-25

PACKAGE LABEL

55 G 76250-101-55

PACKAGE LABEL

275 G 76250-101-75

PACKAGE LABEL

330 G 76250-101-33